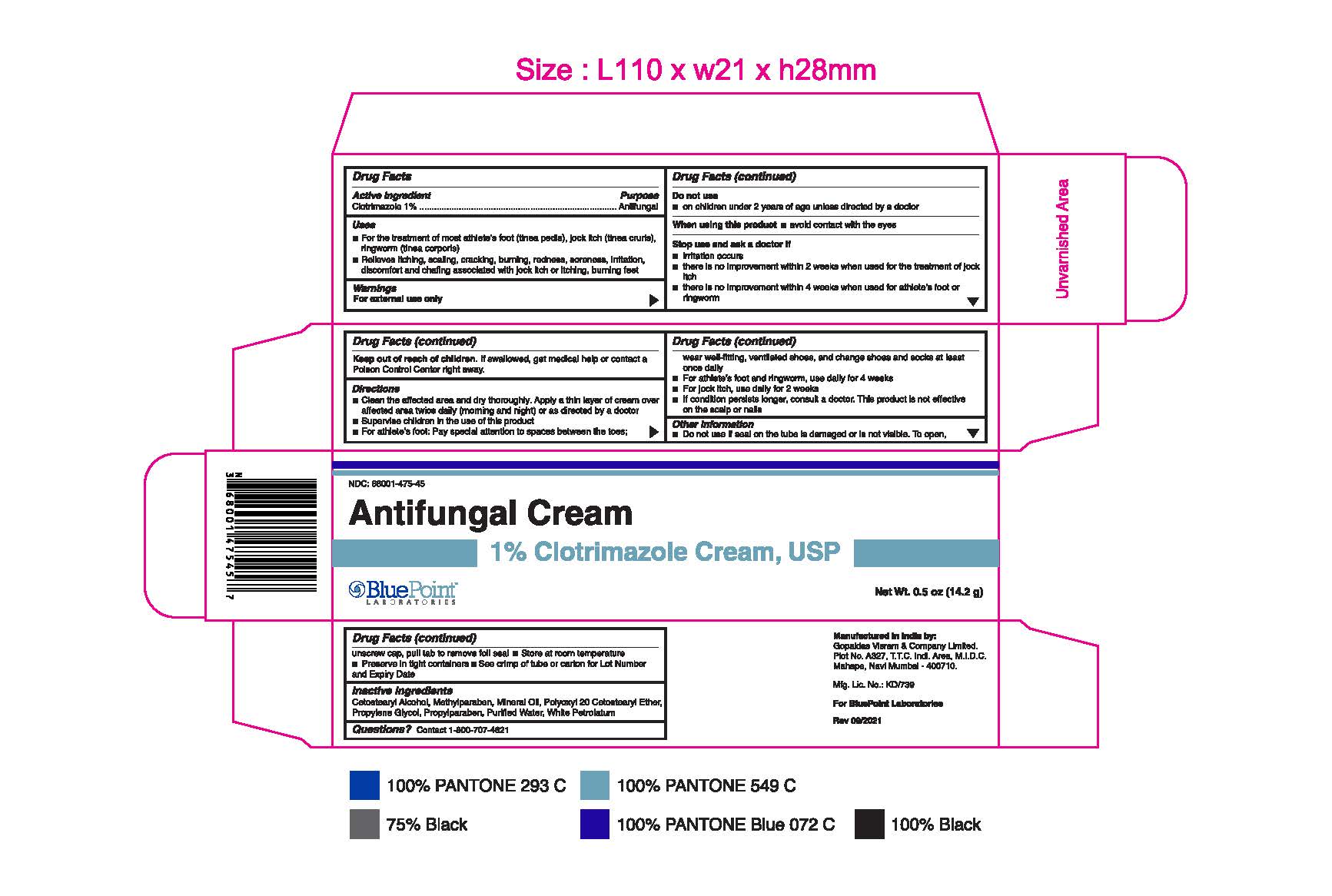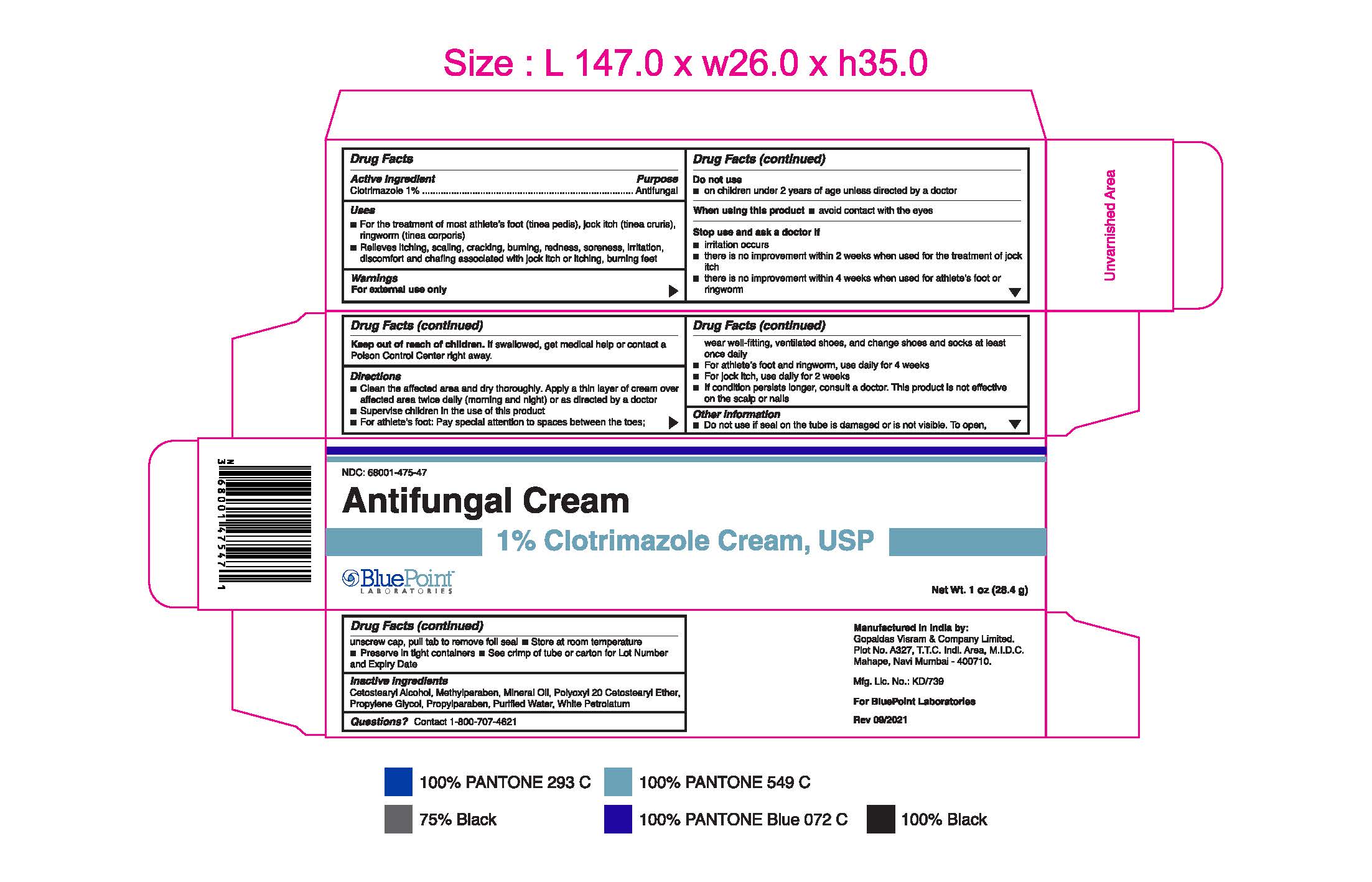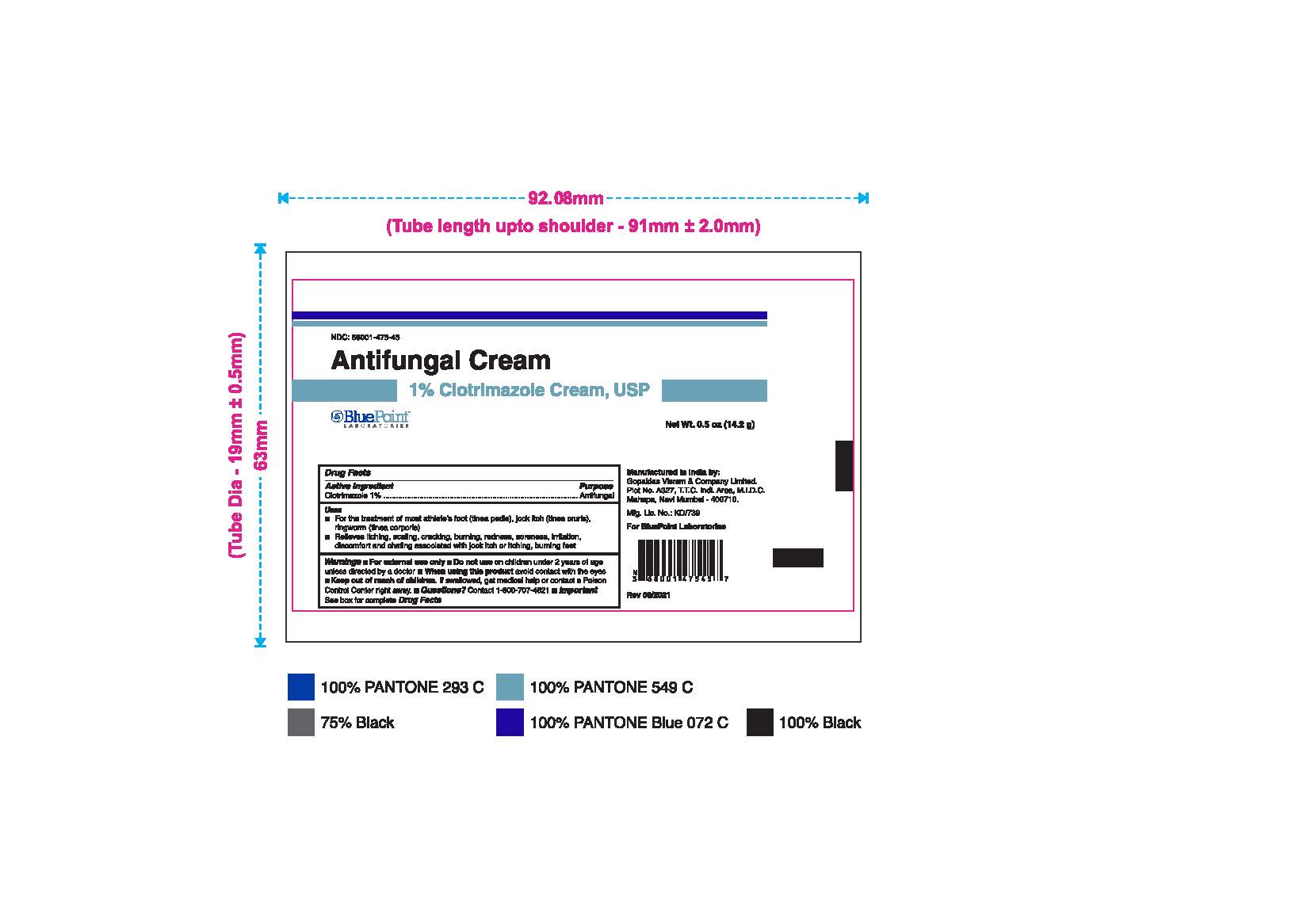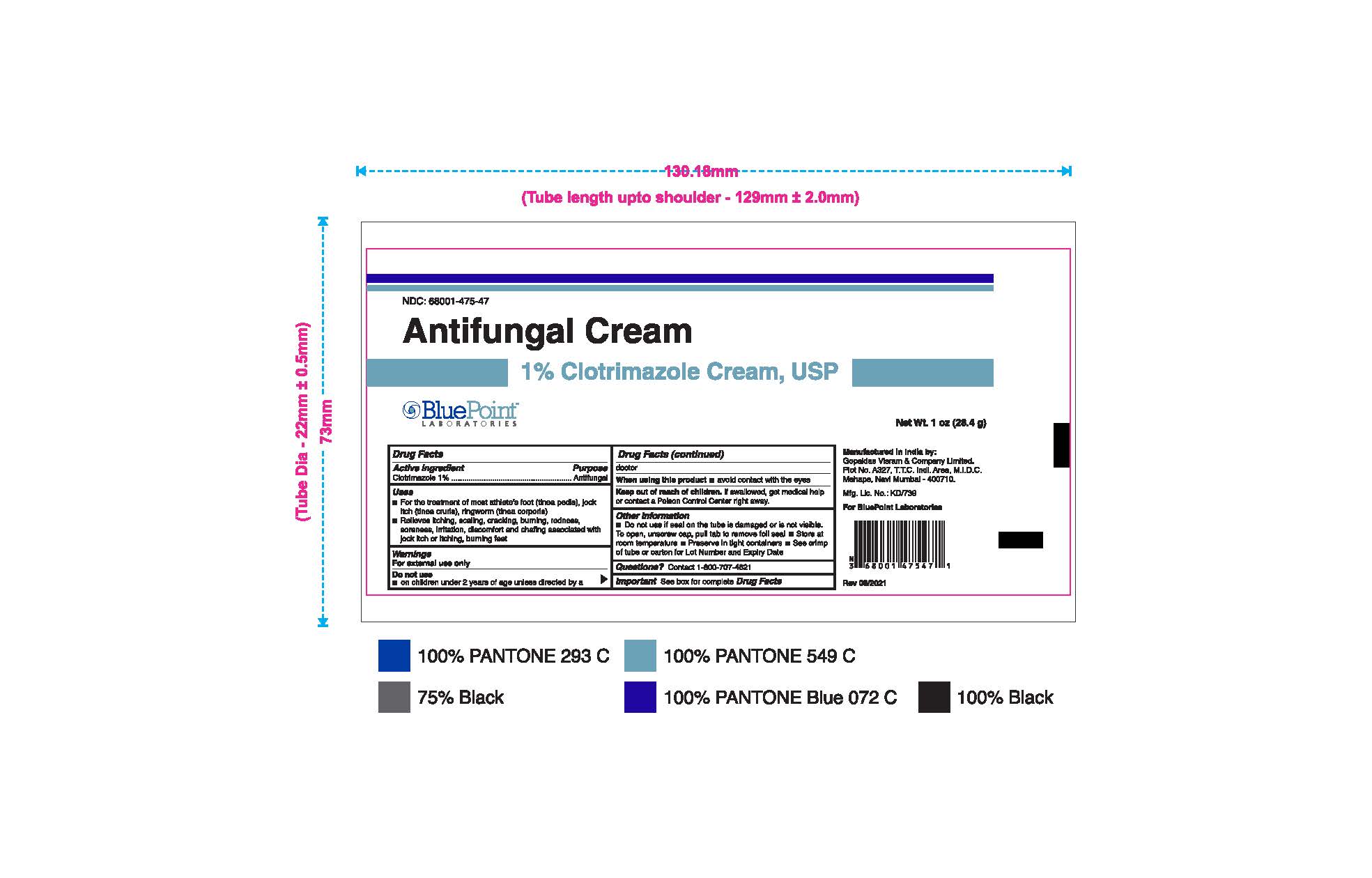 DRUG LABEL: Antifungal Cream
NDC: 68001-475 | Form: CREAM
Manufacturer: BluePoint Laboratories
Category: otc | Type: HUMAN OTC DRUG LABEL
Date: 20231117

ACTIVE INGREDIENTS: CLOTRIMAZOLE 1 g/100 g
INACTIVE INGREDIENTS: PROPYLPARABEN; WATER; WHITE PETROLATUM; POLYOXYL 20 CETOSTEARYL ETHER; MINERAL OIL; CETOSTEARYL ALCOHOL; METHYLPARABEN; PROPYLENE GLYCOL

1 % Clotrimazole Cream, USP

Drug Facts

Active ingredient

Clotrimazole 1 %

Purpose

Antifungal

Uses

- For the treatment of most athlete's foot (tinea pedis), jock itch (tinea cruris), ringworm (tinea corporis).
- Relieves itching, scaling, cracking, burning, redness, soreness, irritation, discomfort and chafing associated with jock itch or itching, burning feet.

Warnings

For external use only

Do not use:

- on children under 2 years of age unless directed by a doctor.

When using this product

- Avoid contact with eyes.

Stop use and ask a doctor if

- irritation occurs
- there is no improvement within 2 weeks when used for the treatment of jock itch.
- there is no improvement within 4 weeks when used for athlete's foot or ringworm.

Keep Out Of Reach Of Children

if swallowed, get medical help or contact a Poison Control Center right away.

Directions

- Clean the affected area and dry thoroughly. Apply a thin layer of cream over affected area twice daily (morning and night) or as directed by a doctor.
- Supervise children in the use of this product.
- For athlete's foot: Pay special attention to spaces between the toes: wear well fitting, ventilated shoes, and change shoes and socks at least once daily.

DOSAGE AND ADMINISTRATION

- For athletes foot and ringworm, use daily for 4 weeks.
- For jock itch, use daily for 2 weeks.
- If condition persists longer, consult a doctor. This product is not effective on the scalp or nails.

Other Information

- Do not use if seal on the tube is damaged or is not visible. To open, unscrew cap, pull tab to remove foil seal
- Store at room temperature
- Preserve in tight containers
- See crimp of tube or carton for Lot Number and Expiry Date

INACTIVE INGREDIENTS

Inactive Ingredients: Cetostearyl Alcohol, Methylparaben, Mineral Oil, Polyoxyl 20 Cetostearyl Ether,

Propylene Glycol, Propylparaben, Purified water, White petrolatum

Questions?

Contact 1-800-707-4621

Manufactured in India by:

Gopaldas Visram & Company Limited,

Plot No. A327, T.T.C. Indl. Area, M.I.D.C.

Mahape, Navi Mumbai - 400710.

Mfg. Lic. No.: KD/739

For BluePoint Laboratories

Rev 09/2021

PACKAGE LABEL

Clotrimazole 1% 0.5oz 68001-475-45

Principal Display Panel

Clotrimazole 1% 1oz 68001-475-47